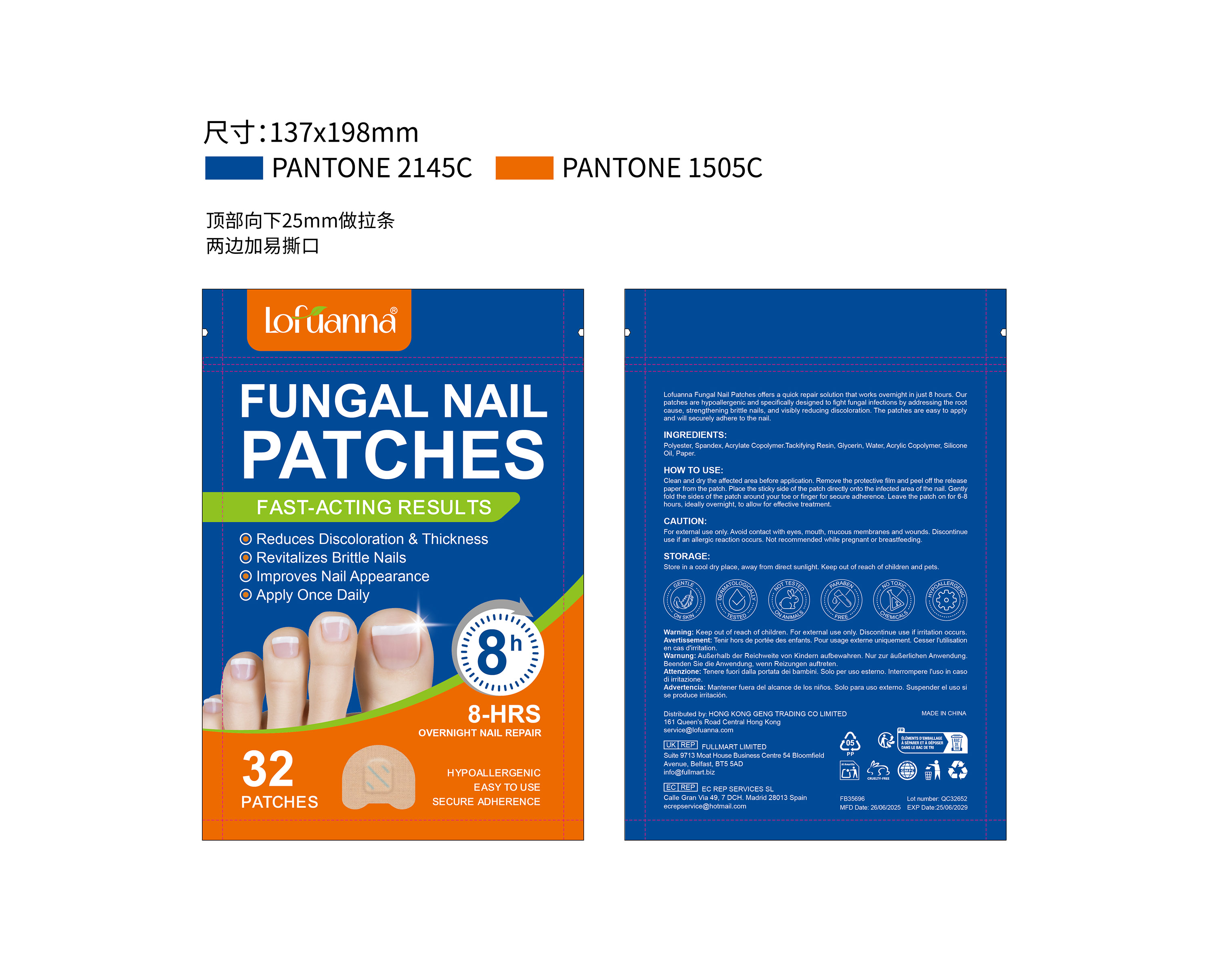 DRUG LABEL: Lofuanna FUNGAL NAIL PATCHES
NDC: 83804-010 | Form: PATCH
Manufacturer: Shenzhen Shandian Jingling Technology Co., Ltd.
Category: otc | Type: HUMAN OTC DRUG LABEL
Date: 20251210

ACTIVE INGREDIENTS: TEA TREE OIL 0.1 g/1 1
INACTIVE INGREDIENTS: WATER; POLYESTER-8 (1400 MW, CYANODIPHENYLPROPENOYL CAPPED); GLYCERIN

83804-010 Lofuanna FUNGAL NAIL PATCHES

ACTIVE INGREDIENT

TEA TREE OIL

PURPOSE

Antifungal

INDICATIONS AND USAGE

Lofuanna Fungal Nail Patches offers a quick repair solution that works overnight in just 8 hours. Ourpatches are hypoallergenic and specifically designed to fight fungal infections by addressing the rootcause, strengthening britle nails, and visibly reducing discoloration. The patches are easy to applyand will securely adhere to the nail.

WARNINGS

For external use only.

Not recommended while pregnant or breastfeeding

WHEN USING

Store in a cool dry place, away from direct sunlight. Keep out of reach of children and pets.

Discontinue use if irritation occurs

Keep out of reach of children.

DOSAGE AND ADMINISTRATION

Clean and dry the affected area before application. Remove the protective film and peel off the releasepaper from the patch. Place the sticky side of the patch directly onto the infected area of the nali. Gentlyfold the sides of the patch around your toe or finger for secure adherence. Leave the patch on for 6-8hours, ideally overnight, to allow for effective treatment.

INACTIVE INGREDIENT

Polyester
WATER
Glycerin